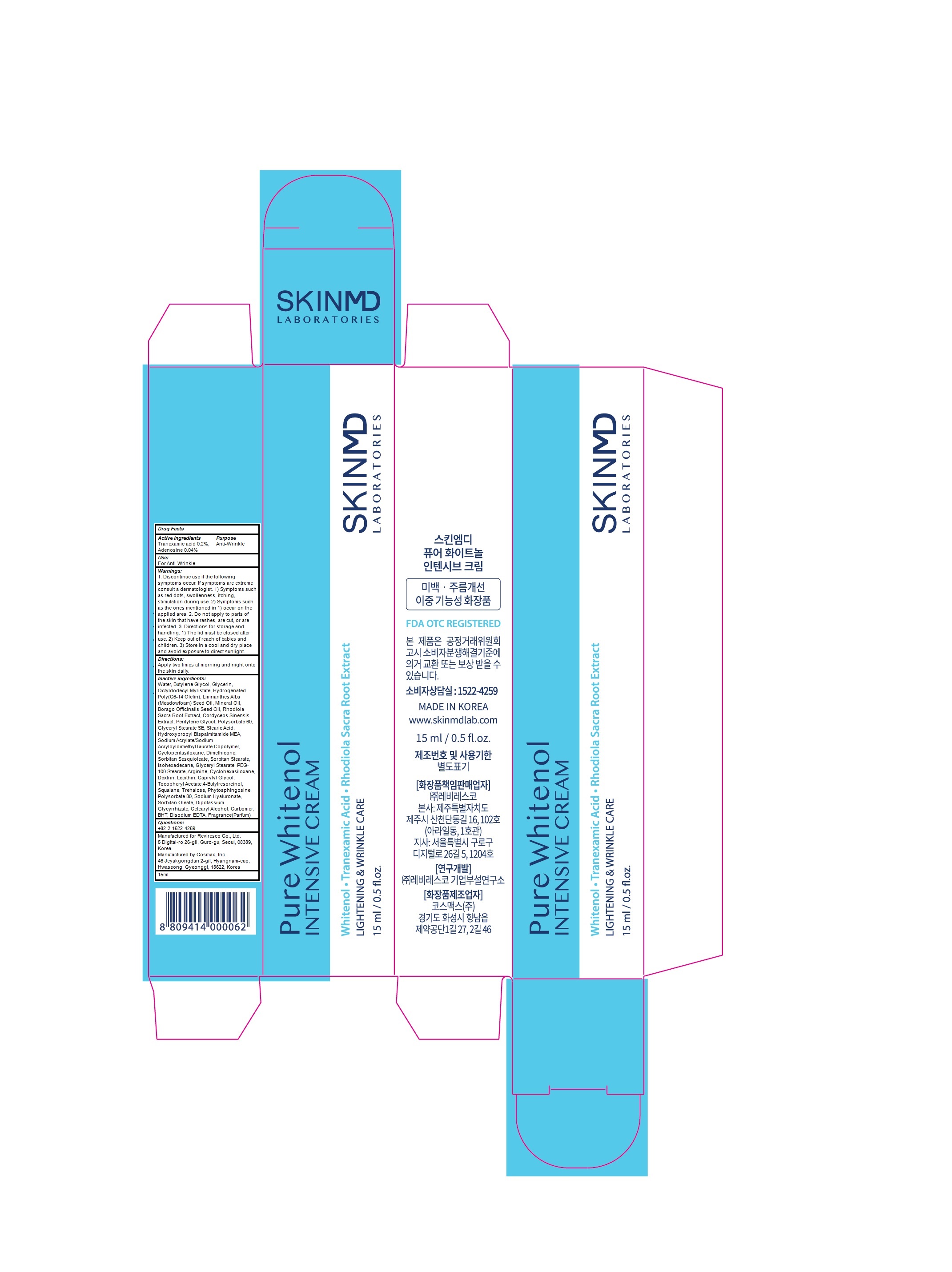 DRUG LABEL: SKINMD LABORATORIES PURE WHITENOL INTENSIVE
NDC: 71974-020 | Form: CREAM
Manufacturer: Reviresco Co., Ltd.
Category: otc | Type: HUMAN OTC DRUG LABEL
Date: 20191224

ACTIVE INGREDIENTS: Tranexamic acid 0.02 g/10 mL; Adenosine 0.004 g/10 mL
INACTIVE INGREDIENTS: Water; Butylene Glycol

ACTIVE INGREDIENT

Active ingredients: Tranexamic acid 0.2%, Adenosine 0.04%

INACTIVE INGREDIENT

Inactive ingredients:

Water, Butylene Glycol, Glycerin, Octyldodecyl Myristate, Hydrogenated Poly(C6-14 Olefin), Limnanthes Alba (Meadowfoam) Seed Oil, Mineral Oil, Borago Officinalis Seed Oil, Rhodiola Sacra Root Extract, Cordyceps Sinensis Extract, Pentylene Glycol, Polysorbate 60, Glyceryl Stearate SE, Stearic Acid, Hydroxypropyl Bispalmitamide MEA, Sodium Acrylate/Sodium AcryloyldimethylTaurate Copolymer, Cyclopentasiloxane, Dimethicone, Sorbitan Sesquioleate, Sorbitan Stearate, Isohexadecane, Glyceryl Stearate, PEG-100 Stearate, Arginine, Cyclohexasiloxane, Dextrin, Lecithin, Caprylyl Glycol, Tocopheryl Acetate,4-Butylresorcinol, Squalane, Trehalose, Phytosphingosine, Polysorbate 80, Sodium Hyaluronate, Sorbitan Oleate, Dipotassium Glycyrrhizate, Cetearyl Alcohol, Carbomer, BHT, Disodium EDTA, Fragrance(Parfum)

PURPOSE

Purpose: Anti wrinkle

WARNINGS

1. Discontinue use if the following symptoms occur. If symptoms are extreme consult a dermatologist. 1) Symptoms such as red dots, swollenness, itching, stimulation during use. 2) Symptoms such as the ones mentioned in 1) occur on the applied area. 2. Do not apply to parts of the skin that have rashes, are cut, or are infected. 3. Directions for storage and handling. 1) The lid must be closed after use. 2) Keep out of reach of babies and children. 3) Store in a cool and dry place and avoid exposure to direct sunlight.

KEEP OUT OF REACH OF CHILDREN

Keep out of reach of babies and children.

Uses

Uses: For anti-wrinkle

Directions

Directions: Apply two times at morning and night onto the skin daily.